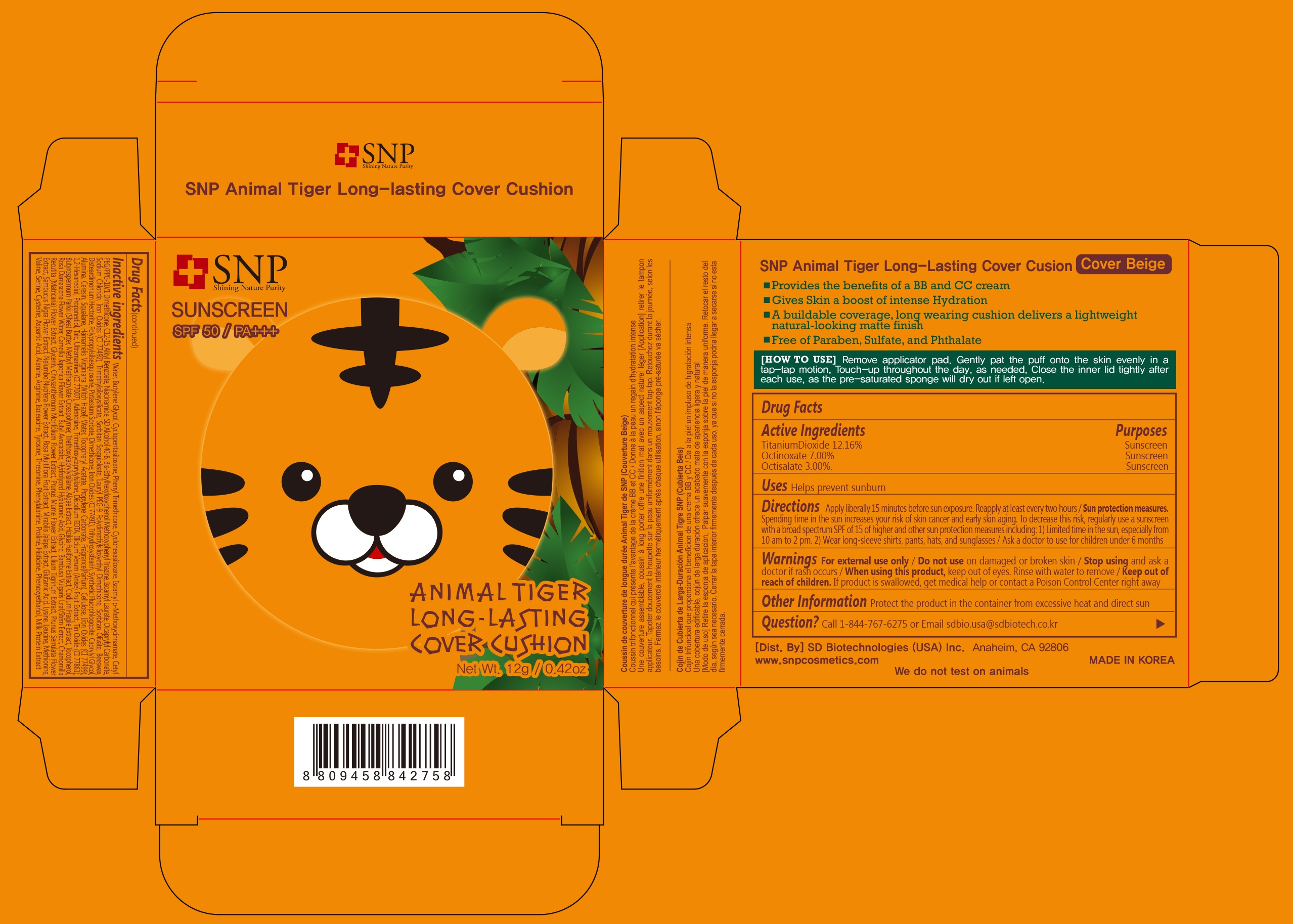 DRUG LABEL: SNP Animal Tiger Long-lasting Cover Cushion
NDC: 70142-002 | Form: CREAM
Manufacturer: SD BIOTECHNOLOGIES CO., LTD
Category: otc | Type: HUMAN OTC DRUG LABEL
Date: 20161016

ACTIVE INGREDIENTS: TITANIUM DIOXIDE 1.4592 g/12 g; OCTINOXATE 0.84 g/12 g; OCTISALATE 0.36 g/12 g
INACTIVE INGREDIENTS: WATER; BUTYLENE GLYCOL; CYCLOMETHICONE 5; PHENYL TRIMETHICONE; CYCLOMETHICONE 6; AMILOXATE; CETYL PEG/PPG-10/1 DIMETHICONE (HLB 2); ALKYL (C12-15) BENZOATE; NIACINAMIDE; ALCOHOL; BEMOTRIZINOL; ISOAMYL LAURATE; DICAPRYLYL CARBONATE; SODIUM CHLORIDE; FERRIC OXIDE YELLOW; TRIMETHYLSILOXYSILICATE (M/Q 0.6-0.8); SORBITAN SESQUIOLEATE; LAURYL PEG-9 POLYDIMETHYLSILOXYETHYL DIMETHICONE; SORBITAN OLIVATE; YELLOW WAX; DISTEARDIMONIUM HECTORITE; POTASSIUM SORBATE; DIMETHICONE; FERRIC OXIDE RED; TRIHYDROXYSTEARIN; CAPRYLYL GLYCOL; ALUMINUM OXIDE; CERESIN; SQUALANE; HAMAMELIS VIRGINIANA TOP WATER; .ALPHA.-TOCOPHEROL ACETATE; PROPYLENE CARBONATE; POWDERED CELLULOSE; FERROSOFERRIC OXIDE; 1,2-HEXANEDIOL; PROPANEDIOL; TALC; ULTRAMARINE BLUE; ADENOSINE; TRIMETHOXYCAPRYLYLSILANE; EDETATE DISODIUM; STAR ANISE FRUIT; STANNIC OXIDE; SHEA BUTTER; TRIETHOXYCAPRYLYLSILANE; PHYMATOLITHON CALCAREUM; SARGASSUM FUSIFORME; CODIUM FRAGILE; TOCOPHEROL; ROSA DAMASCENA FLOWER OIL; CAMELLIA JAPONICA FLOWER; GLYCINE; BAMBUSA VULGARIS TOP; CHAMOMILE; GLYCERIN; CHRYSANTHEMUM X MORIFOLIUM FLOWER; PRUNUS MUME FLOWER; LILIUM LANCIFOLIUM BULB; PRUNUS SERRULATA FLOWER; SAMBUCUS NIGRA FLOWER; NELUMBO NUCIFERA FLOWER; ROSA MULTIFLORA FRUIT; MIRABILIS JALAPA SEED; GLUTAMIC ACID; LYSINE; LEUCINE; METHIONINE; VALINE; SERINE; CYSTEINE; ASPARTIC ACID; ALANINE; ARGININE; ISOLEUCINE; TYROSINE; THREONINE; PHENYLALANINE; PROLINE; HISTIDINE; PHENOXYETHANOL; CASEIN

Drug Facts

ACTIVE INGREDIENT

Titanium Dioxide 12.16%
Octinoxate 7.00%
Octisalate 3.00%

PURPOSE

Sunscreen

INDICATIONS AND USAGE

Helps prevent sunburn

DOSAGE AND ADMINISTRATION

Apply liberally 15 minutes before sun exposure. Reapply at least every two hours

Sun protection measures. Spending time in the sun increases your risk of skin cancer and early skin aging. To decrease this risk, regularly use a sunscreen with a broad spectrum SPF of 15 of higher and other sun protection measures including: 1) Limited time in the sun, especially from 10 am to 2 pm. 2) Wear long-sleeve shirts, pants, hats, and sunglasses

Ask a doctor to use for children under 6 months

WARNINGS

For external use only

Do not use on damaged or broken skin

When using this product, keep out of eyes. Rinse with water to remove.

Stop using and ask a doctor if rash occurs.

KEEP OUT OF REACH OF CHILDREN

Keep out of reach of the children. If product is swallowed, get medical help or contact a poison control center right away.

INACTIVE INGREDIENT

Water, Butylene Glycol, Cyclopentasiloxane, Phenyl Trimethicone, Cyclohexasiloxane, Isoamyl p-Methoxycinnamate, Cetyl PEG/PPG-10/1 Dimethicone, C12-15 Alkyl Benzoate, Niacinamide, SD Alcohol 40-B, Bis-Ethylhexyloxyphenol Methoxyphenyl Triazine, Isoamyl Laurate, Dicaprylyl Carbonate, Sodium Chloride, Iron Oxides (CI 77492), Trimethylsiloxysilicate, Sorbitan Sesquioleate, Lauryl PEG-9 Polydimethylsiloxyethyl Dimethicone, Sorbitan Olivate, Beeswax, Disteardimonium Hectorite, Polypropylsilsesquioxane, Potassium Sorbate, Dimethicone, Iron Oxides (CI 77491), Trihydroxystearin, Synthetic Fluorphlogopite, Caprylyl Glycol, Alumina, Squalane, Hamamelis Virginiana (Witch Hazel) Water, Tocopheryl Acetate, Propylene Carbonate, Fragrance(Parfum), Cellulose, Iron Oxides (CI 77499), 1,2-Hexanediol, Propanediol, Talc, Ultramarines (CI 77007), Adenosine, Trimethoxycaprylylsilane, Disodium EDTA, Illicium Verum (Anise) Fruit Extract, Tin Oxide (CI 77861), Butyrospermum Parkii (Shea) Butter, Methyl Methacrylate Crosspolymer, Triethoxycaprylylsilane, Algae Extract, Hizikia Fusiforme Extract, Codium Fragile Extract, Tocopherol, Rosa Damascena Flower Water, Camellia Japonica Flower Extract, Butyl Avocadate, Hydrolyzed Hyaluronic Acid, Glycine, Bambusa Vulgaris Leaf/Stem Extract, Chamomilla Recutita (Matricaria) Flower Extract, Glycerin, Chrysanthemum Morifolium Flower Extract, Prunus Mume Flower Extract, Lilium Tigrinum Extract, Prunus Serrulata Flower Extract, Sambucus Nigra Flower Extract, Nelumbo Nucifera Flower Extract, Rosa Multiflora Fruit Extract, Mirabilis Jalapa Extract, Glutamic Acid, Lysine, Leucine, Methionine, Valine, Serine, Cysteine, Aspartic Acid, Alanine, Arginine, Isoleucine, Tyrosine, Threonine, Phenylalanine, Proline, Histidine, Phenoxyethanol, Milk Protein Extract

OTHER SAFETY INFORMATION

Protect the product in the container from excessive heat and direct sun

QUESTIONS

Call 1-844-767-6275 or Email sdbio.usa@sdbiotech.co.kr